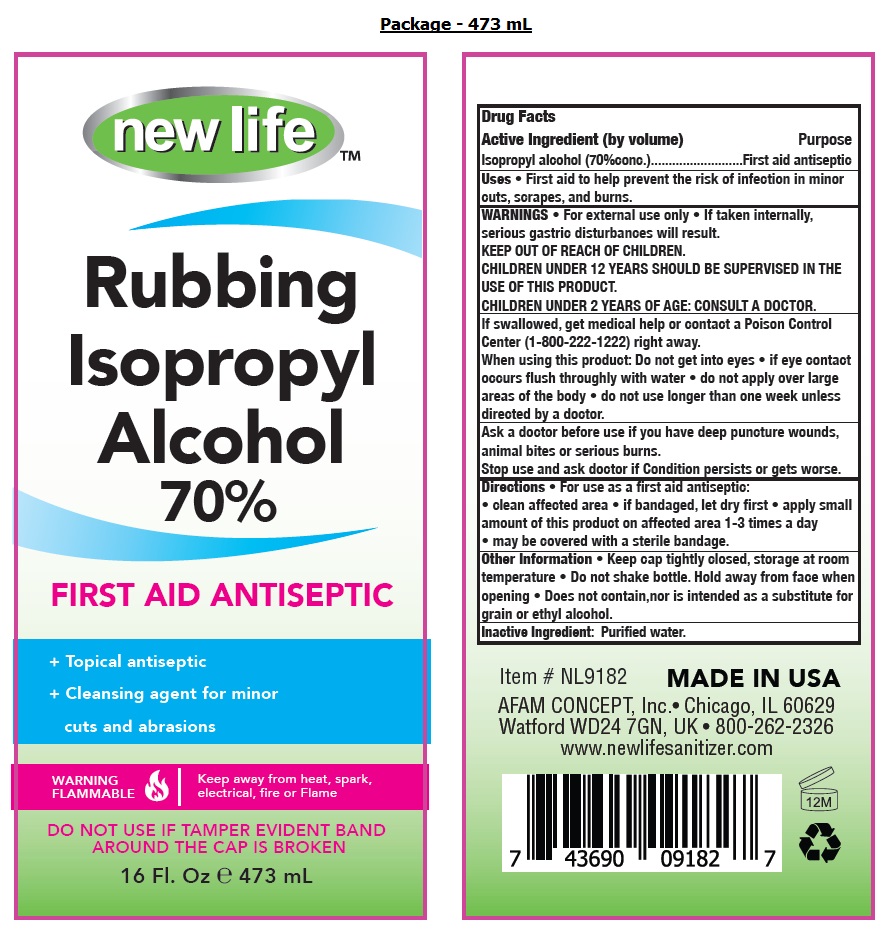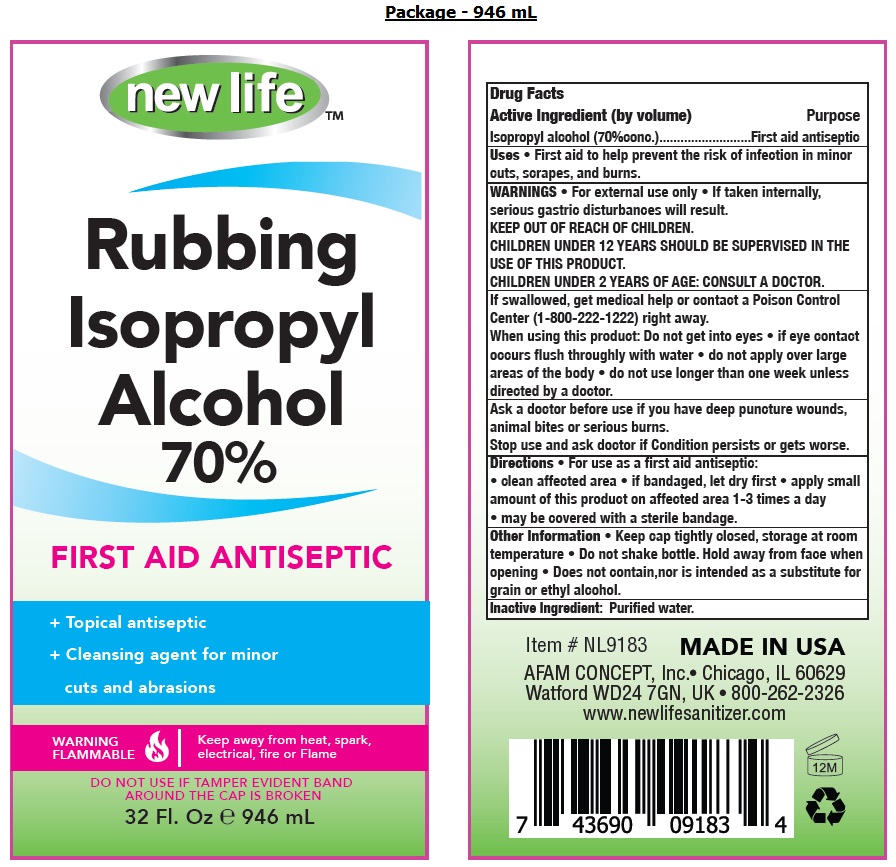 DRUG LABEL: new life Rubbing Isopropyl Alcohol 70% First Aid and Antiseptic
NDC: 49681-014 | Form: LIQUID
Manufacturer: New Life Products, Inc.
Category: otc | Type: HUMAN OTC DRUG LABEL
Date: 20230202

ACTIVE INGREDIENTS: ISOPROPYL ALCOHOL 70 mL/100 mL
INACTIVE INGREDIENTS: WATER

new lifeTM Rubbing Isopropyl Alcohol 70% FIRST AID ANTISEPTIC

Active Ingredient (by volume)

Isopropyl alcohol (70%conc.)

Purpose

First aid antiseptic

Uses

• First aid to help prevent the risk of infection in minor cuts, scrapes, and burns.

WARNINGS

• For external use only • If taken internally, serious gastric disturbances will result.

CHILDREN UNDER 12 YEARS SHOULD BE SUPERVISED IN THE USE OF THIS PRODUCT.

CHILDREN UNDER 2 YEARS OF AGE: CONSULT A DOCTOR.

When using this product: Do not get into eyes • if eye contact occurs flush thoroughly with water. • do not apply over large areas of the body • do not use longer than one week unless directed by a doctor.

Ask a doctor before use if you have deep puncture wounds, animal bites or serious burns.

Stop use and ask doctor if Condition persists or gets worse.

KEEP OUT OF REACH OF CHILDREN.

If swallowed, get medical help or contact a Poison Control Center (1-800-222-1222) right away.

Directions

• For use as a first aid antiseptic:

• clean affected area • if bandaged, let dry first • apply small amount of this product on affected area 1-3 times a day • may be covered with a sterile bandage.

Other Information

• Keep cap tightly closed, storage at room temperature. • Do not shake bottle. Hold away from face when opening • Does not contain, nor is intended as a substitute for grain or ethyl alcohol.

Inactive Ingredient:

Purified water.

+ Topical antiseptic

+ Cleansing agent for minor cuts and abrasions

WARNING FLAMMABLE

Keep away from heat, spark, electrical, fire or Flame

DO NOT USE IF TAMPER EVIDENT BAND AROUND THE CAP IS BROKEN

MADE IN USA

AFAM CONCEPT, Inc. • Chicago, IL 60629

Watford WD24 7GN, UK • 800-262-2326

www.newlifesanitizer.com